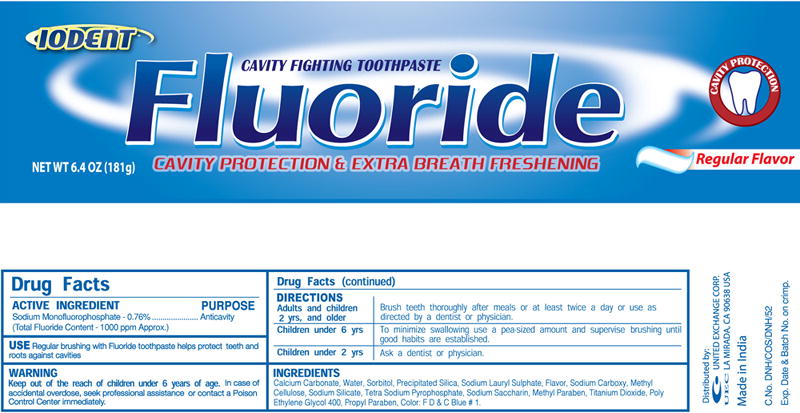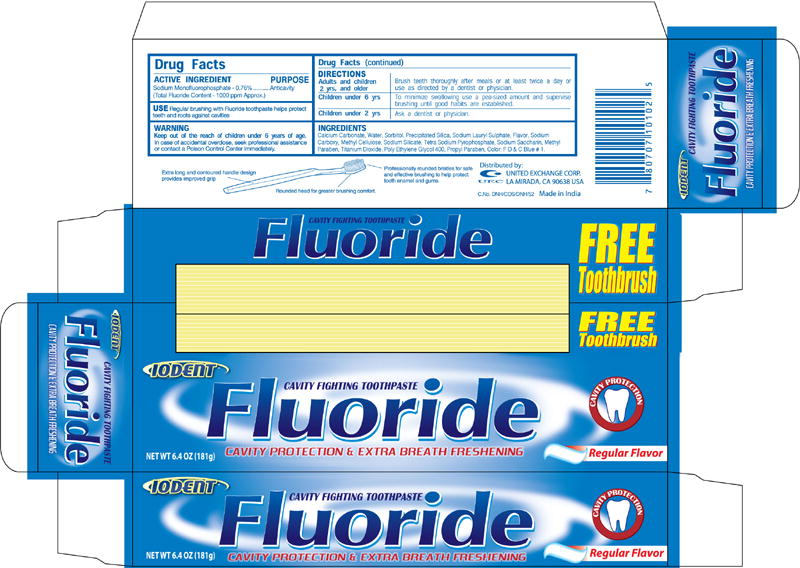 DRUG LABEL: Iodent Fluoride Toothpaste
NDC: 68747-6029 | Form: PASTE, DENTIFRICE
Manufacturer: Dabur India Limited
Category: otc | Type: HUMAN OTC DRUG LABEL
Date: 20080825

ACTIVE INGREDIENTS: SODIUM MONOFLUOROPHOSPHATE 7.6 mg/1 g
INACTIVE INGREDIENTS: CALCIUM CARBONATE; WATER; SORBITOL; SILICON DIOXIDE; SODIUM LAURYL SULFATE; CARBOXYMETHYLCELLULOSE SODIUM; SODIUM SILICATE; SODIUM PYROPHOSPHATE; SACCHARIN SODIUM; TITANIUM DIOXIDE; METHYLPARABEN; POLYETHYLENE GLYCOL 400; PROPYLPARABEN

Iodent Fluoride Toothpaste

ACTIVE INGREDIENT

Sodium Monofluorophosphate -0.76%

(Total Fluoride Content -1000 ppm Approx.)

PURPOSE

Anticavity

USE

Regular brushing with Fluoride toothpaste helps protect
teeth and roots against cavities

WARNING

Keep out of the reach of children under 6 years of age.

In case of accidental overdose, seek professional assistance or contact a Poison Control Center immediately.

Drug Facts (continued)

DIRECTIONS

Adults and children 2 yrs, and older

Brush teeth thoroughly after meals or at least twice a day or use as directed by a dentist or physician.

Children under 6 yrs

To minimize swallowing use a pea-sized amount and supervise brushing until good habits are established.

Children under 2 yrs

Ask a dentist or physician.

INGREDIENTS

Calcium Carbonate, Water, Sorbitol, Precipitated Silica, Sodium Lauryl Sulphate, Flavor, Sodium
Carboxy, Methyl Cellulose, Sodium Silicate, Tetra Sodium Pyrophosphate, Sodium Saccharin, Methyl
Paraben, Titanium Dioxide, Poly Ethylene Glycol 400, Propyl Paraben, Color: F D & C Blue # 1.

Fluoride Toothpaste Tube Label
FREE
Toothbrush
IODENTTM
CAVITY FIGHTING TOOTHPASTE
Fluoride
CAVITY PROTECTION & EXTRA RREATH FRESHENING
NET WT 6.4 OZ(181g)

CAVITY PROTECION

Regular Flavor

Fluoride Toothpaste Carton Label
FREE
Toothbrush
IODENTTM
CAVITY FIGHTING TOOTHPASTE
Fluoride
CAVITY PROTECTION & EXTRA RREATH FRESHENING
NET WT 6.4 OZ(181g)

CAVITY PROTECION

Regular Flavor